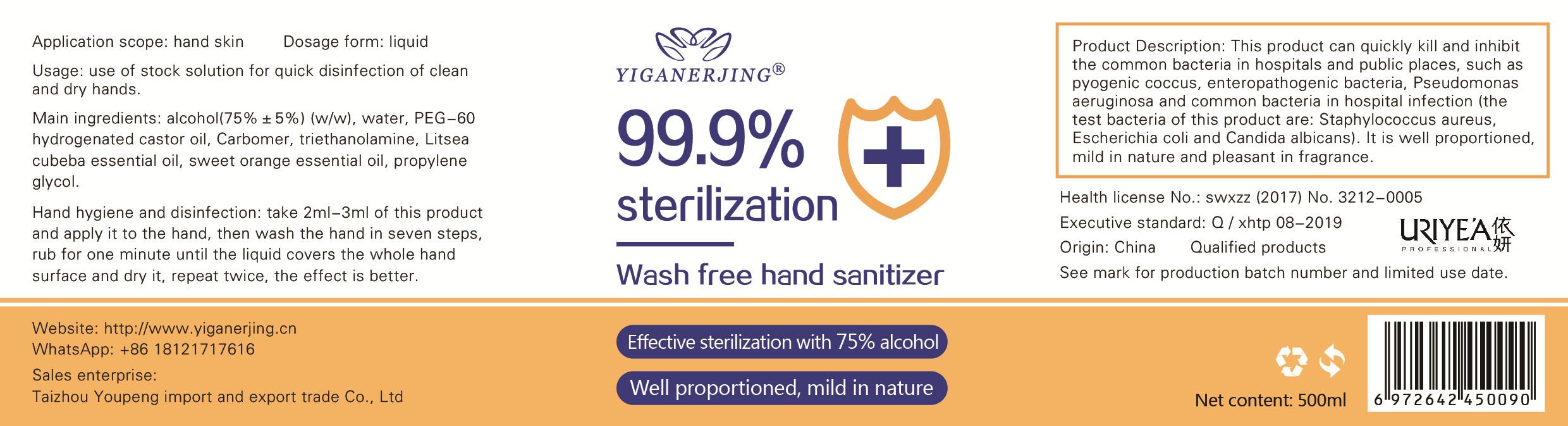 DRUG LABEL: YIGANERJING  Wash Free Hand Sanitizer
NDC: 71939-002 | Form: LIQUID
Manufacturer: TAIZHOU YOUPENG IMPORT AND EXPORT TRADING CO.,LTD.
Category: otc | Type: HUMAN OTC DRUG LABEL
Date: 20220310

ACTIVE INGREDIENTS: PEG-60 HYDROGENATED CASTOR OIL 1.2 g/500 mL; PROPYLENE GLYCOL 0.5 g/500 mL; TROLAMINE 2.5 g/500 mL; CARBOMER HOMOPOLYMER, UNSPECIFIED TYPE 2.25 g/500 mL; ALCOHOL 375 mL/500 mL
INACTIVE INGREDIENTS: WATER

DOSAGE AND ADMINISTRATION

Store in a cool and dry place

INACTIVE INGREDIENT

Water,Litseacubeba essential oil, sweet orange essential oil

INDICATIONS AND USAGE

Hand hygiene and disinfection: take 2ml-3ml of this produc and apply it to the hand, then wash the hand in seven steps
rub for one minute until the liquid covers the whole hand surface and dry it, repeat twice, the effect is better.

ACTIVE INGREDIENT

alcohol,PEG-60 hydrogenated castor oil,Propylene glycol,triethanolamine,Carbomer

keep out of reach of children

PURPOSE

Disinfection
Sterilization

WARNINGS

For external use only. Flammable. Keep away from heat or flame